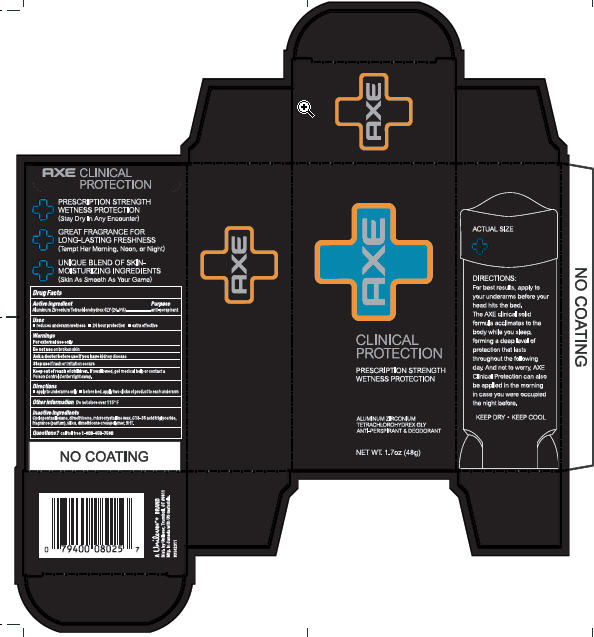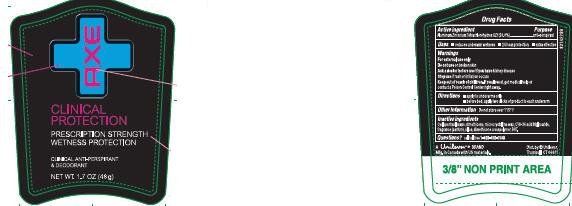 DRUG LABEL: Axe Clinical Protection
NDC: 64942-1116 | Form: STICK
Manufacturer: Conopco Inc. d/b/a Unilever
Category: otc | Type: HUMAN OTC DRUG LABEL
Date: 20100111

ACTIVE INGREDIENTS: Aluminum Zirconium Tetrachlorohydrex GLY 20 g/100 g

Front and Back PDP Axe Clinical Protection AP and Deod., PDP, outer carton and drug facts

Active Ingredient Purpose

Aluminum Zirconium Tetrachlorohydrex GLY (20%).................anti-perspirant

Warnings For External Use only

INACTIVE INGREDIENT

Cyclopentasiloxane, Dimethicone, Microcrystalline Wax, C18-36 Acid Triglyceride, Fragrance (Parfum), Silica, Dimethicone Crosspolymer, BHT.

Questions? Call toll-free 1-800-450-7580

Do not use on broken skin

Ask a doctor before use if you have kidney disease

Stop use if rash or irritation occurs

Keep out of reach of children. If swallowed, get medical help or contact a Poison Control Center right away.

PACKAGE LABEL

PDP 1.7oz

PACKAGE LABEL

Outer Carton PDP 1.7 oz